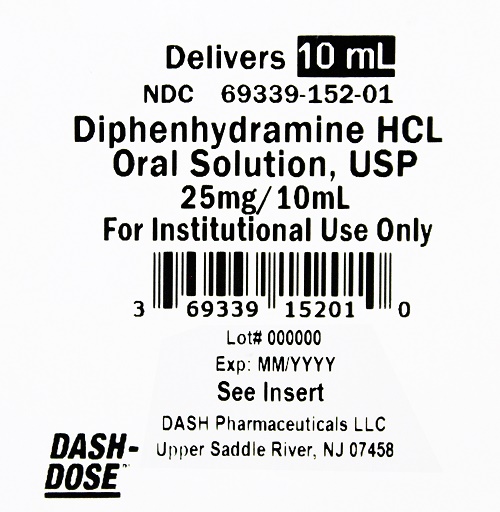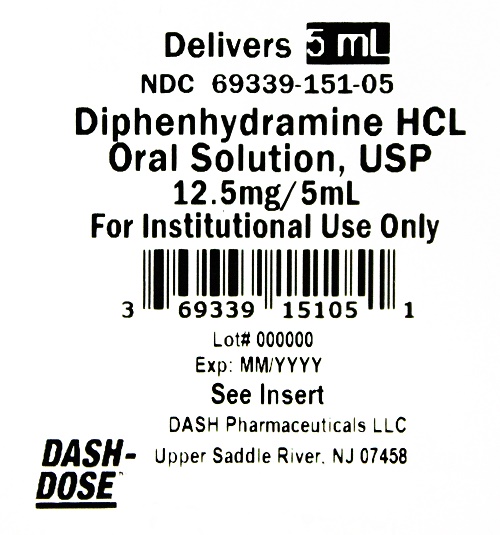 DRUG LABEL: Diphenhydramine HCl Oral Solution
NDC: 69339-151 | Form: SOLUTION
Manufacturer: Natco Pharma USA LLC
Category: otc | Type: HUMAN OTC DRUG LABEL
Date: 20231101

ACTIVE INGREDIENTS: DIPHENHYDRAMINE HYDROCHLORIDE 12.5 mg/5 mL
INACTIVE INGREDIENTS: ANHYDROUS CITRIC ACID; GLYCERIN; WATER; SUCROSE; SODIUM BENZOATE; SODIUM CITRATE, UNSPECIFIED FORM; D&C RED NO. 33; FD&C RED NO. 40; POLOXAMER 407; SODIUM CHLORIDE

Diphenydramine HCl Oral Solution, USP

Drug Facts

Active ingredient (in each 5 mL)

Diphenhydramine HCl USP 12.5 mg

Active ingredient (in each 10 mL)

Diphenhydramine HCl USP 25 mg

Purpose

Antihistamine

Uses

temporarily relieves these symptoms due to hay fever or other upper respiratory allergies: • runny nose • sneezing • itchy, watery eyes • itchy throat

Warnings

Do not use

• in neonates or premature infants • if pregnant or breast-feeding • if hypersensitive to diphenhydramine HCI and other similar antihistamine • with any other product containing diphenhydramine, even one used on skin • to make a child sleepy

Ask a doctor before use if you have

• glaucoma • a breathing problem such as emphysema or chronic bronchitis
• a sodium restricted diet • trouble urinating due to enlarged prostate gland

Ask a doctor or pharmacist before use if you are taking tranquilizers or sedatives

When using this product

• marked drowsiness may occur • avoid alcoholic drinks • alcohol, sedatives, and tranquilizers may increase drowsiness
• be careful when driving a motor vehicle or operating machinery • excitability may occur, especially in children

Keep out of reach of children.

In case of overdose, get medical help or contact a Poison Control Center right away (1-800-222-1222)

Directions

• Use the following dosage guidelines when using this product

Age (yr) | Dose (mL)
Adults and children 12 years and older | take 10 mL every 4 to 6 hours; not more than 60 mL in 24 hours.
Children 6 years to under 12 years | take 5 mL every 4 to 6 hours; not more than 30 mL in 24 hours
Children under 6 years | ask a doctor

Other information

• each 5mL contains sodium 10mg
• each 10mL contains sodium 20mg
• alcohol free, cherry flavor
• store at 20-25°C (68-77°F)
• protect from excessive moisture
• do not use if lid seal is open or damaged
• see top of cup for lot number and expiration date

Inactive ingredients

Citric acid, D&C Red No. 33, FD&C Red No. 40, flavor, glycerin, poloxamer 407, purified water, sodium benzoate, sodium chloride, sodium citrate,
and sucrose.

How Supplied

Each 5 mL of Diphenhydramine Hydrochloride Oral Solution, USP contains 12.5mg diphenhydramine hydrochloride and is supplied in the following oral dosage forms:

NDC 69339-151-05 (1) unit dose cup 5mL
NDC 69339-151-17 40 (4x10) unit dose cups 5mL
NDC 69339-151-19 100 (10x10) unit dose cups 5mL

Each 10 mL of Diphenhydramine Hydrochloride Oral Solution, USP contains 25mg diphenhydramine hydrochloride and is supplied in the following oral dosage forms:

NDC 69339-152-01 (1) unit dose cup 10mL
NDC 69339-152-17 40 (4x10) unit dose cups 10mL
NDC 69339-152-19 100 (10x10) unit dose cups 10mL

Questions or comments?

Call 201-786-6500

Dash Pharmaceuticals LLC
Upper Saddle River, NJ 07458

DP-UD-PI-AT-[117894] Rev 08/20

PRINCIPAL DISPLAY PANEL

Delivers 5 mL

NDC 69339-151-05

Diphenydramine HCl Oral Solution, USP

12.5 mg/5 mL

For Institutional Use Only

3 69339 15105 1

Lot # 000000

Exp: MM/YYY

See Insert

DASH Pharmaceuticals LLC

Upper Saddle River, NJ 07458

DASH-

DOSE

PRINCIPAL DISPLAY PANEL

Delivers 10 mL

NDC 69339-152-01

Diphenydramine HCl Oral Solution, USP

25 mg/10 mL

For Institutional Use Only

3 69339 15201 0

Lot # 000000

Exp: MM/YYY

See Insert

DASH Pharmaceuticals LLC

Upper Saddle River, NJ 07458

DASH-

DOSE